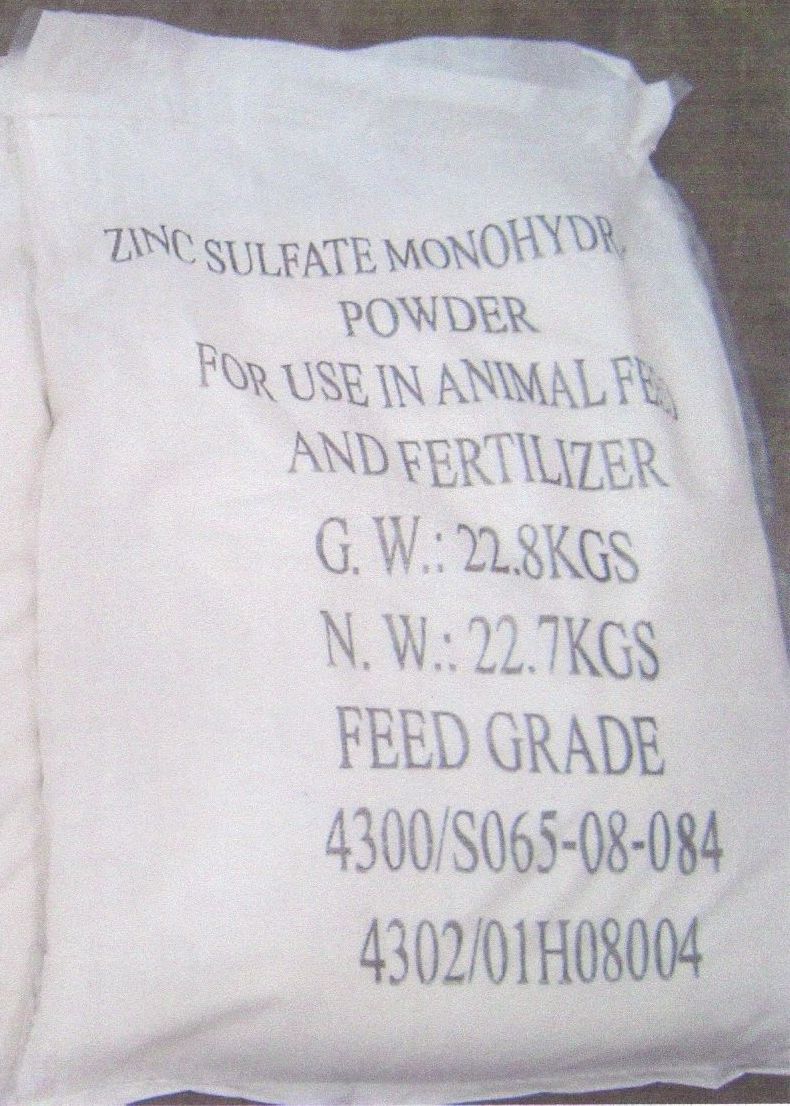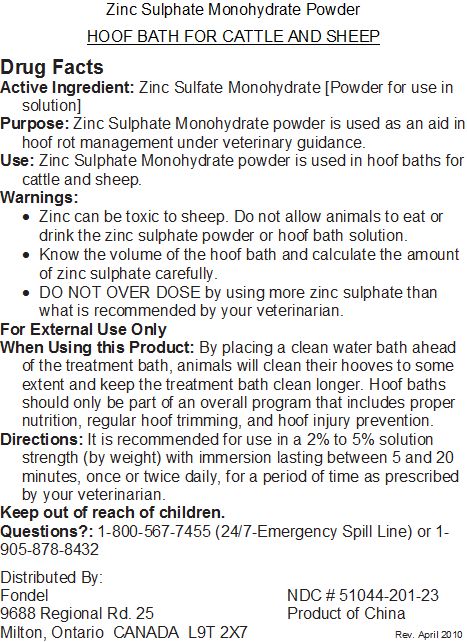 DRUG LABEL: Zinc Sulfate Monohydrate
NDC: 51044-201 | Form: POWDER, FOR SOLUTION
Manufacturer: Fondel Chemicals Ltd.
Category: animal | Type: OTC ANIMAL DRUG LABEL
Date: 20100702

ACTIVE INGREDIENTS: Zinc Sulfate Monohydrate 0.4 kg/1.6 kg

Zinc Sulfate Monohydrate Label

Active Ingredient: Zinc Sulfate Monohydrate [Powder for use in solution]

PURPOSE

Purpose:Zinc Sulphate Monohydrate powder is used as an aid in hoof rot management under veterinary guidance.

Warnings:

- Zinc can be toxic to sheep. Do not allow animals to eat or drink the zinc sulphate powder or hoof bath solution.
- Know the volume of the hoof bath and calculate the amount of zinc sulphate carefully.
- Do not overdose by using more zinc sulphate than what is recommended by your veterinarian.

For External Use Only

When Using this Product: By placing a clean water bath ahead of the treatment bath, animals will clean their hooves to some extent and keep the treatment bath clean longer. Hoof baths should only be part of an overall program that includes proper nutrition, regular hoof trimming, and hoof injury prevention.

Keep out of reach of children.

QUESTIONS

Questions?: 1-800-567-7455 (24/7-Emergency Spill Line) or 1-905-878-8432

Zinc Sulfate Monhydrate Directions, Distributor Contact Information and Country of Origin

Directions: It is recommended for use in a 2% to 5% solution strength (by weight) with immersion lasting between 5 and 20 minutes, once or twice daily, for a period of time as prescribed by your veterinarian.

Distributed By:

Fondel Chemicals Ltd.

9688 Regional Rd. 25

Milton, Ontario CANADA L9T 2X7

Product of China

PACKAGE LABEL

Enter section text here